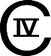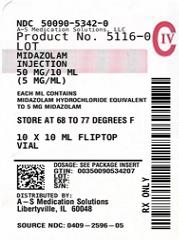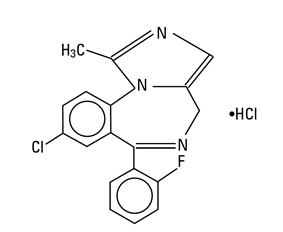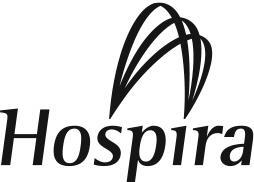 DRUG LABEL: Midazolam Hydrochloride
NDC: 50090-5342 | Form: INJECTION, SOLUTION
Manufacturer: A-S Medication Solutions
Category: prescription | Type: HUMAN PRESCRIPTION DRUG LABEL
Date: 20260123
DEA Schedule: CIV

ACTIVE INGREDIENTS: MIDAZOLAM HYDROCHLORIDE 5 mg/1 mL
INACTIVE INGREDIENTS: SODIUM CHLORIDE 8 mg/1 mL; EDETATE DISODIUM 0.1 mg/1 mL; BENZYL ALCOHOL 10 mg/1 mL; HYDROCHLORIC ACID; SODIUM HYDROXIDE

Midazolam
Injection, USP

Rx only

For intravenous or intramuscular use.

NOT FOR USE IN NEONATES

CONTAINS BENZYL ALCOHOL

WARNINGS

Personnel and Equipment for Monitoring and Resuscitation

Adults and Pediatrics: Intravenous midazolam has been associated with respiratory depression and respiratory arrest, especially when used for sedation in noncritical care settings. In some cases, where this was not recognized promptly and treated effectively, death or hypoxic encephalopathy has resulted. Intravenous midazolam should be used only in hospital or ambulatory care settings, including physicians' and dental offices, that provide for continuous monitoring of respiratory and cardiac function, e.g., pulse oximetry. Immediate availability of resuscitative drugs and age- and size-appropriate equipment for bag/valve/mask ventilation and intubation, and personnel trained in their use and skilled in airway management should be assured (see WARNINGS). For deeply sedated pediatric patients, a dedicated individual, other than the practitioner performing the procedure, should monitor the patient throughout the procedure.

Risks From Concomitant Use With Opioids

Concomitant use of benzodiazepines and opioids may result in profound sedation, respiratory depression, coma, and death. Monitor patients for respiratory depression and sedation (see WARNINGS and PRECAUTIONS; Drug Interactions).

Individualization of Dosage

Midazolam must never be used without individualization of dosage. The initial intravenous dose for sedation in adult patients may be as little as 1 mg, but should not exceed 2.5 mg in a normal healthy adult. Lower doses are necessary for older (over 60 years) or debilitated patients and in patients receiving concomitant narcotics or other central nervous system (CNS) depressants. The initial dose and all subsequent doses should always be titrated slowly; administer over at least 2 minutes and allow an additional 2 or more minutes to fully evaluate the sedative effect. The use of the 1 mg/mL formulation or dilution of the 1 mg/mL or 5 mg/mL formulation is recommended to facilitate slower injection. Doses of sedative medications in pediatric patients must be calculated on a mg/kg basis, and initial doses and all subsequent doses should always be titrated slowly. The initial pediatric dose of midazolam for sedation/anxiolysis/amnesia is age, procedure, and route dependent (see DOSAGE AND ADMINISTRATION for complete dosing information).

Neonates: Midazolam should not be administered by rapid injection in the neonatal population. Severe hypotension and seizures have been reported following rapid intravenous administration, particularly with concomitant use of fentanyl (see DOSAGE AND ADMINISTRATION for complete information).

DESCRIPTION

Midazolam hydrochloride injection is a water-soluble benzodiazepine available as a sterile, nonpyrogenic parenteral dosage form for intravenous or intramuscular injection. Each mL contains midazolam hydrochloride equivalent to 1 mg or 5 mg midazolam compounded with 0.8% sodium chloride and 0.01% disodium edetate, with 1% benzyl alcohol as preservative; the pH is adjusted to approximately 3 with hydrochloric acid and, if necessary, sodium hydroxide.

Midazolam is a white to light yellow crystalline compound, insoluble in water. The hydrochloride salt of midazolam, which is formed in situ, is soluble in aqueous solutions. Chemically, midazolam HCl is 8-chloro-6-(2-fluorophenyl)-1-methyl-4H-imidazo[1,5-a][1,4]benzodiazepine hydrochloride. Midazolam hydrochloride has the empirical formula C18H13ClFN3∙HCl, a calculated molecular weight of 362.24 and the following structural formula:

CLINICAL PHARMACOLOGY

Pharmacodynamics:

Midazolam is a short-acting benzodiazepine central nervous system (CNS) depressant.

The effects of midazolam on the CNS are dependent on the dose administered, the route of administration, and the presence or absence of other medications. Onset time of sedative effects after intramuscular administration in adults is 15 minutes, with peak sedation occurring 30 to 60 minutes following injection. In one adult study, when tested the following day, 73% of the patients who received midazolam intramuscularly had no recall of memory cards shown 30 minutes following drug administration; 40% had no recall of the memory cards shown 60 minutes following drug administration. Onset time of sedative effects in the pediatric population begins within 5 minutes and peaks at 15 to 30 minutes depending upon the dose administered. In pediatric patients, up to 85% had no recall of pictures shown after receiving intramuscular midazolam compared with 5% of the placebo controls.

Sedation in adult and pediatric patients is achieved within 3 to 5 minutes after intravenous injection; the time of onset is affected by total dose administered and the concurrent administration of narcotic premedication. Seventy-one percent of the adult patients in endoscopy studies had no recall of introduction of the endoscope; 82% of the patients had no recall of withdrawal of the endoscope. In one study of pediatric patients undergoing lumbar puncture or bone marrow aspiration, 88% of patients had impaired recall vs 9% of the placebo controls. In another pediatric oncology study, 91% of midazolam treated patients were amnestic compared with 35% of patients who had received fentanyl alone.

When midazolam is given intravenous as an anesthetic induction agent, induction of anesthesia occurs in approximately 1.5 minutes when narcotic premedication has been administered and in 2 to 2.5 minutes without narcotic premedication or other sedative premedication. Some impairment in a test of memory was noted in 90% of the patients studied. A dose response study of pediatric patients premedicated with 1 mg/kg intramuscular meperidine found that only 4 out of 6 pediatric patients who received 600 mcg/kg intravenous midazolam lost consciousness, with eye closing at 108 ±140 seconds. This group was compared with pediatric patients who were given thiopental 5 mg/kg intravenous; 6 out of 6 closed their eyes at 20 ± 3.2 seconds. Midazolam did not dependably induce anesthesia at this dose despite concomitant opioid administration in pediatric patients.

Midazolam, used as directed, does not delay awakening from general anesthesia in adults. Gross tests of recovery after awakening (orientation, ability to stand and walk, suitability for discharge from the recovery room, return to baseline Trieger competency) usually indicate recovery within 2 hours but recovery may take up to 6 hours in some cases. When compared with patients who received thiopental, patients who received midazolam generally recovered at a slightly slower rate. Recovery from anesthesia or sedation for procedures in pediatric patients depends on the dose of midazolam administered, coadministration of other medications causing CNS depression and duration of the procedure.

In patients without intracranial lesions, induction of general anesthesia with intravenous midazolam is associated with a moderate decrease in cerebrospinal fluid pressure (lumbar puncture measurements), similar to that observed following intravenous thiopental. Preliminary data in neurosurgical patients with normal intracranial pressure but decreased compliance (subarachnoid screw measurements) show comparable elevations of intracranial pressure with midazolam and with thiopental during intubation. No similar studies have been reported in pediatric patients.

The usual recommended intramuscular premedicating doses of midazolam do not depress the ventilatory response to carbon dioxide stimulation to a clinically significant extent in adults. Intravenous induction doses of midazolam depress the ventilatory response to carbon dioxide stimulation for 15 minutes or more beyond the duration of ventilatory depression following administration of thiopental in adults. Impairment of ventilatory response to carbon dioxide is more marked in adult patients with chronic obstructive pulmonary disease (COPD). Sedation with intravenous midazolam does not adversely affect the mechanics of respiration (resistance, static recoil, most lung volume measurements); total lung capacity and peak expiratory flow decrease significantly but static compliance and maximum expiratory flow at 50% of awake total lung capacity (Vmax) increase. In one study of pediatric patients under general anesthesia, intramuscular midazolam (100 g/kg or 200 g/kg) was shown to depress the response to carbon dioxide in a dose-related manner.

In cardiac hemodynamic studies in adults, intravenous induction of general anesthesia with midazolam was associated with a slight to moderate decrease in mean arterial pressure, cardiac output, stroke volume and systemic vascular resistance. Slow heart rates (less than 65/minute), particularly in patients taking propranolol for angina, tended to rise slightly; faster heart rates (e.g., 85/minute) tended to slow slightly. In pediatric patients, a comparison of intravenous midazolam (500 g/kg) with propofol (2.5 mg/kg) revealed a mean 15% decrease in systolic blood pressure in patients who had received intravenous midazolam vs a mean 25% decrease in systolic blood pressure following propofol.

Pharmacokinetics:

Midazolam's activity is primarily due to the parent drug. Elimination of the parent drug takes place via hepatic metabolism of midazolam to hydroxylated metabolites that are conjugated and excreted in the urine. Six single-dose pharmacokinetic studies involving healthy adults yield pharmacokinetic parameters for midazolam in the following ranges: volume of distribution (Vd), 1.0 to 3.1 L/kg; elimination half-life, 1.8 to 6.4 hours (mean approximately 3 hours); total clearance (Cl), 0.25 to 0.54 L/hr/kg. In a parallel group study, there was no difference in the clearance, in subjects administered 0.15 mg/kg (n=4) and 0.3 mg/kg (n=4) intravenous doses indicating linear kinetics. The clearance was successively reduced by approximately 30% at doses of 0.45 mg/kg (n=4) and 0.6 mg/kg (n=5) indicating non-linear kinetics in this dose range.

Absorption: The absolute bioavailability of the intramuscular route was greater than 90% in a cross-over study in which healthy subjects (n=17) were administered a 7.5 mg intravenous or intramuscular dose. The mean peak concentration (Cmax) and time to peak (Tmax) following the intramuscular dose was 90 ng/mL (20% cv) and 0.5 hour (50% cv). Cmax for the 1-hydroxy metabolite following the intramuscular dose was 8 ng/mL (Tmax=1.0 hour).

Following intramuscular administration, Cmax for midazolam and its 1-hydroxy metabolite were approximately one-half of those achieved after intravenous injection.

Distribution: The volume of distribution (Vd) determined from six single-dose pharmacokinetic studies involving healthy adults ranged from 1.0 to 3.1 L/kg. Female gender, old age, and obesity are associated with increased values of midazolam Vd. In humans, midazolam has been shown to cross the placenta and enter into fetal circulation and has been detected in human milk and CSF (see CLINICAL PHARMACOLOGY, Special Populations).

In adults and pediatric patients older than 1 year, midazolam is approximately 97% bound to plasma protein, principally albumin and that for 1-hydroxy metabolite is about 89%.

Metabolism: In vitro studies with human liver microsomes indicate that the biotransformation of midazolam is mediated by cytochrome P450-3A4. This cytochrome also appears to be present in gastrointestinal tract mucosa as well as liver. Sixty to seventy percent of the biotransformation products is 1-hydroxy-midazolam (also termed alpha-hydroxymidazolam) while 4-hydroxy-midazolam constitutes 5% or less. Small amounts of a dihydroxy derivative have also been detected but not quantified. The principal urinary excretion products are glucuronide conjugates of the hydroxylated derivatives.

Drugs that inhibit the activity of cytochrome P450-3A4 may inhibit midazolam clearance and elevate steady-state midazolam concentrations.

Studies of the intravenous administration of 1-hydroxy-midazolam in humans suggest that 1-hydroxy-midazolam is at least as potent as the parent compound and may contribute to the net pharmacologic activity of midazolam. In vitro studies have demonstrated that the affinities of 1- and 4-hydroxy-midazolam for the benzodiazepine receptor are approximately 20% and 7%, respectively, relative to midazolam.

Excretion: Clearance of midazolam is reduced in association with old age, congestive heart failure, liver disease (cirrhosis) or conditions which diminish cardiac output and hepatic blood flow.

The principal urinary excretion product is 1-hydroxy-midazolam in the form of a glucuronide conjugate; smaller amounts of the glucuronide conjugates of 4-hydroxy- and dihydroxy-midazolam are detected as well. The amount of midazolam excreted unchanged in the urine after a single intravenous dose is less than 0.5% (n=5). Following a single intravenous infusion in 5 healthy volunteers, 45% to 57% of the dose was excreted in the urine as 1-hydroxymethyl midazolam conjugate.

Pharmacokinetics-Continuous Infusion: The pharmacokinetic profile of midazolam following continuous infusion, based on 282 adult subjects, has been shown to be similar to that following single-dose administration for subjects of comparable age, gender, body habitus and health status. However, midazolam can accumulate in peripheral tissues with continuous infusion. The effects of accumulation are greater after long-term infusions than after short-term infusions. The effects of accumulation can be reduced by maintaining the lowest midazolam infusion rate that produces satisfactory sedation.

Infrequent hypotensive episodes have occurred during continuous infusion; however, neither the time to onset nor the duration of the episode appeared to be related to plasma concentrations of midazolam or alpha-hydroxy-midazolam. Further, there does not appear to be an increased chance of occurrence of a hypotensive episode with increased loading doses.

Patients with renal impairment may have longer elimination half-lives for midazolam (see CLINICAL PHARMACOLOGY, Special Populations: Renal Failure).

Special Populations:

Changes in the pharmacokinetic profile of midazolam due to drug interactions, physiological variables, etc., may result in changes in the plasma concentration-time profile and pharmacological response to midazolam in these patients. For example, patients with acute renal failure appear to have a longer elimination half-life for midazolam and may experience delayed recovery (see CLINICAL PHARMACOLOGY, Special Populations: Renal Failure). In other groups, the relationship between prolonged half-life and duration of effect has not been established.

Pediatrics and Neonates: In pediatric patients aged 1 year and older, the pharmacokinetic properties following a single dose of midazolam reported in 10 separate studies of midazolam are similar to those in adults. Weight-normalized clearance is similar or higher (0.19 to 0.80 L/hr/kg) than in adults and the terminal elimination half-life (0.78 to 3.3 hours) is similar to or shorter than in adults. The pharmacokinetic properties during and following continuous intravenous infusion in pediatric patients in the operating room as an adjunct to general anesthesia and in the intensive care environment are similar to those in adults.

In seriously ill neonates, however, the terminal elimination half-life of midazolam is substantially prolonged (6.5 to 12.0 hours) and the clearance reduced (0.07 to 0.12 L/hr/kg) compared to healthy adults or other groups of pediatric patients. It cannot be determined if these differences are due to age, immature organ function or metabolic pathways, underlying illness or debility.

Obese: In a study comparing normals (n=20) and obese patients (n=20) the mean half-life was greater in the obese group (5.9 vs 2.3 hours). This was due to an increase of approximately 50% in the Vd corrected for total body weight. The clearance was not significantly different between groups.

Geriatric: In three parallel group studies, the pharmacokinetics of midazolam administered intravenously or intramuscularly were compared in young (mean age 29, n=52) and healthy elderly subjects (mean age 73, n=53). Plasma half-life was approximately two-fold higher in the elderly. The mean Vd based on total body weight increased consistently between 15% to 100% in the elderly. The mean Cl decreased approximately 25% in the elderly in two studies and was similar to that of the younger patients in the other.

Congestive Heart Failure: In patients suffering from congestive heart failure, there appeared to be a two-fold increase in the elimination half-life, a 25% decrease in the plasma clearance and a 40% increase in the volume of distribution of midazolam.

Hepatic Impairment: Midazolam pharmacokinetics were studied after an intravenous single dose (0.075 mg/kg) was administered to 7 patients with biopsy proven alcoholic cirrhosis and 8 control patients. The mean half-life of midazolam increased 2.5-fold in the alcoholic patients. Clearance was reduced by 50% and the Vd increased by 20%. In another study in 21 male patients with cirrhosis, without ascites and with normal kidney function as determined by creatinine clearance, no changes in the pharmacokinetics of midazolam or 1-hydroxy-midazolam were observed when compared to healthy individuals.

Renal Impairment: Patients with renal impairment may have longer elimination half-lives for midazolam and its metabolites which may result in slower recovery.

Midazolam and 1-hydroxy-midazolam pharmacokinetics in 6 ICU patients who developed acute renal failure (ARF) were compared with a normal renal function control group. Midazolam was administered as an infusion (5 to 15 mg/hours). Midazolam clearance was reduced (1.9 vs 2.8 mL/min/kg) and the half-life was prolonged (7.6 vs 13 hr) in the ARF patients. The renal clearance of the 1-hydroxy-midazolam glucuronide was prolonged in the ARF group (4 vs 136 mL/min) and the half-life was prolonged (12 hours vs >25 hours). Plasma levels accumulated in all ARF patients to about ten times that of the parent drug. The relationship between accumulating metabolite levels and prolonged sedation is unclear.

In a study of chronic renal failure patients (n=15) receiving a single intravenous dose, there was a two-fold increase in the clearance and volume of distribution but the half-life remained unchanged. Metabolite levels were not studied.

Plasma Concentration-Effect Relationship: Concentration-effect relationships (after an intravenous dose) have been demonstrated for a variety of pharmacodynamic measures (eg, reaction time, eye movement, sedation) and are associated with extensive intersubject variability. Logistic regression analysis of sedation scores and steady-state plasma concentration indicated that at plasma concentrations greater than 100 ng/mL there was at least a 50% probability that patients would be sedated, but respond to verbal commands (sedation score = 3). At 200 ng/mL there was at least a 50% probability that patients would be asleep, but respond to glabellar tap (sedation score = 4).

Drug Interactions: For information concerning pharmacokinetic drug interactions with midazolam (see PRECAUTIONS).

INDICATIONS AND USAGE

Midazolam injection is indicated:

- intramuscularly or intravenously for preoperative sedation/anxiolysis/amnesia;
- intravenously as an agent for sedation/anxiolysis/amnesia prior to or during diagnostic, therapeutic or endoscopic procedures, such as bronchoscopy, gastroscopy, cystoscopy, coronary angiography, cardiac catheterization, oncology procedures, radiologic procedures, suture of lacerations and other procedures either alone or in combination with other CNS depressants;
- intravenously for induction of general anesthesia, before administration of other anesthetic agents. With the use of narcotic premedication, induction of anesthesia can be attained within a relatively narrow dose range and in a short period of time. Intravenous midazolam can also be used as a component of intravenous supplementation of nitrous oxide and oxygen (balanced anesthesia);
- continuous intravenous infusion for sedation of intubated and mechanically ventilated patients as a component of anesthesia or during treatment in a critical care setting.

CONTRAINDICATIONS

Injectable midazolam is contraindicated in patients with a known hypersensitivity to the drug. Benzodiazepines are contraindicated in patients with acute narrow-angle glaucoma. Benzodiazepines may be used in patients with open-angle glaucoma only if they are receiving appropriate therapy. Measurements of intraocular pressure in patients without eye disease show a moderate lowering following induction with midazolam; patients with glaucoma have not been studied.

Midazolam is not intended for intrathecal or epidural administration due to the presence of the preservative benzyl alcohol in the dosage form. Midazolam injection is contraindicated for use in premature infants because the formulation contains benzyl alcohol (see WARNINGS and PRECAUTIONS, Pediatric Use).

WARNINGS

Personnel and Equipment for Monitoring and Resuscitation

Prior to the intravenous administration of midazolam in any dose, the immediate availability of oxygen, resuscitative drugs, age- and size-appropriate equipment for bag/valve/mask ventilation and intubation, and skilled personnel for the maintenance of a patent airway and support of ventilation should be ensured. Patients should be continuously monitored for early signs of hypoventilation, airway obstruction, or apnea, with means readily available (e.g., pulse oximetry). Hypoventilation, airway obstruction, and apnea can lead to hypoxia and/or cardiac arrest unless effective countermeasures are taken immediately. The immediate availability of specific reversal agents (flumazenil) is highly recommended. Vital signs should continue to be monitored during the recovery period. Because intravenous midazolam can depress respiration (see CLINICAL PHARMACOLOGY), especially when used concomitantly with opioid agonists and other sedatives (see DOSAGE AND ADMINISTRATION), it should be used for sedation/anxiolysis/amnesia only in the presence of personnel skilled in early detection of hypoventilation, maintaining a patent airway and supporting ventilation. When used for sedation/anxiolysis/amnesia, midazolam should always be titrated slowly in adult or pediatric patients. Adverse hemodynamic events have been reported in pediatric patients with cardiovascular instability; rapid intravenous administration should also be avoided in this population (see DOSAGE AND ADMINISTRATION for complete information).

Risks from Concomitant Use With Opioids

Concomitant use of benzodiazepines, including midazolam, and opioids may result in profound sedation, respiratory depression, coma, and death. If a decision is made to use midazolam concomitantly with opioids, monitor patients closely for respiratory depression and sedation (see PRECAUTIONS; Drug Interactions).

Risk of Respiratory Adverse Events

Serious cardiorespiratory adverse events have occurred after administration of midazolam. These have included respiratory depression, airway obstruction, oxygen desaturation, apnea, respiratory arrest and/or cardiac arrest, sometimes resulting in death or permanent neurologic injury. There have also been rare reports of hypotensive episodes requiring treatment during or after diagnostic or surgical manipulations particularly in adult or pediatric patients with hemodynamic instability. Hypotension occurred more frequently in the sedation studies in patients premedicated with a narcotic.

Individualization of Dosage

Midazolam must never be used without individualization of dosage particularly when used with other medications capable of producing central nervous system depression.

See DOSAGE AND ADMINISTRATION for complete information.

Other Adverse Events

Reactions such as agitation, involuntary movements (including tonic/clonic movements and muscle tremor), hyperactivity and combativeness have been reported in both adult and pediatric patients. These reactions may be due to inadequate or excessive dosing or improper administration of midazolam; however, consideration should be given to the possibility of cerebral hypoxia or true paradoxical reactions. Should such reactions occur, the response to each dose of midazolam and all other drugs, including local anesthetics, should be evaluated before proceeding. Reversal of such responses with flumazenil has been reported in pediatric patients.

Concomitant Use of Central Nervous System Depressants

Concomitant use of barbiturates, alcohol or other central nervous system depressants may increase the risk of hypoventilation, airway obstruction, desaturation, or apnea and may contribute to profound and/or prolonged drug effect. Narcotic premedication also depresses the ventilatory response to carbon dioxide stimulation.

Debilitation and Comorbid Considerations

Higher risk adult and pediatric surgical patients, elderly patients and debilitated adult and pediatric patients require lower dosages, whether or not concomitant sedating medications have been administered. Adult or pediatric patients with COPD are unusually sensitive to the respiratory depressant effect of midazolam. Pediatric and adult patients undergoing procedures involving the upper airway such as upper endoscopy or dental care, are particularly vulnerable to episodes of desaturation and hypoventilation due to partial airway obstruction. Adult and pediatric patients with chronic renal failure and patients with congestive heart failure eliminate midazolam more slowly (see CLINICAL PHARMACOLOGY). Because elderly patients frequently have inefficient function of one or more organ systems and because dosage requirements have been shown to decrease with age, reduced initial dosage of midazolam is recommended, and the possibility of profound and/or prolonged effect should be considered.

Injectable midazolam should not be administered to adult or pediatric patients in shock or coma, or in acute alcohol intoxication with depression of vital signs. Particular care should be exercised in the use of intravenous midazolam in adult or pediatric patients with uncompensated acute illnesses, such as severe fluid or electrolyte disturbances.

Risk of Intra-arterial Injection

There have been limited reports of intra-arterial injection of midazolam. Adverse events have included local reactions, as well as isolated reports of seizure activity in which no clear causal relationship was established. Precautions against unintended intra-arterial injection should be taken. Extravasation should also be avoided.

The safety and efficacy of midazolam following nonintravenous and nonintramuscular routes of administration have not been established. Midazolam should only be administered intramuscularly or intravenously.

Return to Full Cognitive Function

Midazolam is associated with a high incidence of partial or complete impairment of recall for the next several hours. The decision as to when patients who have received injectable midazolam, particularly on an outpatient basis, may again engage in activities requiring complete mental alertness, operate hazardous machinery or drive a motor vehicle must be individualized. Gross tests of recovery from the effects of midazolam (see CLINICAL PHARMACOLOGY) cannot be relied upon to predict reaction time under stress. It is recommended that no patient operate hazardous machinery or a motor vehicle until the effects of the drug, such as drowsiness, have subsided or until 1 full day after anesthesia and surgery, whichever is longer. For pediatric patients, particular care should be taken to assure safe ambulation.

Neonatal Sedation and Withdrawal Syndrome

Use of midazolam late in pregnancy can result in sedation (respiratory depression, lethargy, hypotonia) and/or withdrawal symptoms (hyperreflexia, irritability, restlessness, tremors, inconsolable crying, and feeding difficulties) in the neonate (see PRECAUTIONS: Pregnancy). Monitor neonates exposed to midazolam during pregnancy or labor for signs of sedation and monitor neonates exposed to midazolam during pregnancy for signs of withdrawal; manage these neonates accordingly.

Exposure to excessive amounts of benzyl alcohol has been associated with toxicity (hypotension, metabolic acidosis), particularly in neonates, and an increased incidence of kernicterus, particularly in small preterm infants. There have been rare reports of deaths, primarily in preterm infants, associated with exposure to excessive amounts of benzyl alcohol. The amount of benzyl alcohol from medications is usually considered negligible compared to that received in flush solutions containing benzyl alcohol. Administration of high dosages of medications (including midazolam) containing this preservative must take into account the total amount of benzyl alcohol administered. The recommended dosage range of midazolam for preterm and term infants includes amounts of benzyl alcohol well below that associated with toxicity; however, the amount of benzyl alcohol at which toxicity may occur is not known. If the patient requires more than the recommended dosages or other medications containing this preservative, the practitioner must consider the daily metabolic load of benzyl alcohol from these combined sources (see WARNINGS and PRECAUTIONS, Pediatric Use).

Pediatric Neurotoxicity: Published animal studies demonstrate that the administration of anesthetic and sedation drugs that block NMDA receptors and/or potentiate GABA activity increase neuronal apoptosis in the developing brain and result in long-term cognitive deficits when used for longer than 3 hours. The clinical significance of these findings is not clear. However, based on the available data, the window of vulnerability to these changes is believed to correlate with exposures in the third trimester of gestation through the first several months of life, but may extend out to approximately three years of age in humans (see PRECAUTIONS, Pregnancy and Pediatric Use and ANIMAL TOXICOLOGY AND/OR PHARMACOLOGY).

Some published studies in children suggest that similar deficits may occur after repeated or prolonged exposures to anesthetic agents early in life and may result in adverse cognitive or behavioral effects. These studies have substantial limitations, and it is not clear if the observed effects are due to the anesthetic/sedation drug administration or other factors such as the surgery or underlying illness.

Anesthetic and sedation drugs are a necessary part of the care of children needing surgery, other procedures, or tests that cannot be delayed, and no specific medications have been shown to be safer than any other. Decisions regarding the timing of any elective procedures requiring anesthesia should take into consideration the benefits of the procedure weighed against the potential risks.

PRECAUTIONS

GENERAL PRECAUTIONS

General: Intravenous doses of midazolam should be decreased for elderly and for debilitated patients (see WARNINGS and DOSAGE AND ADMINISTRATION). These patients will also probably take longer to recover completely after midazolam administration for the induction of anesthesia.

Midazolam does not protect against the increase in intracranial pressure or against the heart rate rise and/or blood pressure rise associated with endotracheal intubation under light general anesthesia.

The efficacy and safety of midazolam in clinical use are functions of the dose administered, the clinical status of the individual patient, and the use of concomitant medications capable of depressing the CNS. Anticipated effects range from mild sedation to deep levels of sedation virtually equivalent to a state of general anesthesia where the patient may require external support of vital functions. Care must be taken to individualize and carefully titrate the dose of midazolam to the patient's underlying medical/surgical conditions, administer to the desired effect being certain to wait an adequate time for peak CNS effects of both midazolam and concomitant medications, and have the personnel and size-appropriate equipment and facilities available for monitoring and intervention (see Boxed WARNING, WARNINGS and DOSAGE AND ADMINISTRATION). Practitioners administering midazolam must have the skills necessary to manage reasonably foreseeable adverse effects, particularly skills in airway management. For information regarding withdrawal (see DRUG ABUSE AND DEPENDENCE).

Information for Patients

To assure safe and effective use of benzodiazepines, the following information and instructions should be communicated to the patient when appropriate:

1. Inform your physician about any alcohol consumption and medicine you are now taking, especially blood pressure medication and antibiotics, including drugs you buy without a prescription. Alcohol has an increased effect when consumed with benzodiazepines; therefore, caution should be exercised regarding simultaneous ingestion of alcohol during benzodiazepine treatment.
2. Inform your physician if you are pregnant or are planning to become pregnant.
3. Inform your physician if you are nursing.
4. Patients should be informed of the pharmacological effects of midazolam, such as sedation and amnesia, which in some patients may be profound. The decision as to when patients who have received injectable midazolam, particularly on an outpatient basis, may again engage in activities requiring complete mental alertness, operate hazardous machinery or drive a motor vehicle must be individualized.
5. Patients receiving continuous infusion of midazolam in critical care settings over an extended period of time, may experience symptoms of withdrawal following abrupt discontinuation.
6. Effect of anesthetic and sedation drugs on early brain development: Studies conducted in young animals and children suggest repeated or prolonged use of general anesthetic or sedation drugs in children younger than 3 years may have negative effects on their developing brains. Discuss with parents and caregivers the benefits, risks, and timing and duration of surgery or procedures requiring anesthetic and sedation drugs.

Pregnancy

Advise pregnant females that use of midazolam late in pregnancy can result in sedation (respiratory depression, lethargy, hypotonia) and/or withdrawal symptoms (hyperreflexia, irritability, restlessness, tremors, inconsolable crying, and feeding difficulties) in newborns (see WARNINGS: Neonatal Sedation and Withdrawal Syndrome and PRECAUTIONS: Pregnancy). Instruct patients to inform their healthcare provider if they are pregnant.

Nursing

Instruct patients to notify their healthcare provider if they are breastfeeding or intend to breastfeed. Instruct breastfeeding patients receiving midazolam to monitor infants for excessive sedation, poor feeding, and poor weight gain, and to seek medical attention if they notice these signs. A lactating woman may consider pumping and discarding breastmilk for at least 4 to 8 hours after receiving midazolam for sedation or anesthesia to minimize drug exposure to a breastfed infant (see PRECAUTIONS: Nursing Mothers).

Drug Interactions

Effect of Concomitant Use of Benzodiazepines and Opioids

The concomitant use of benzodiazepines and opioids increases the risk of respiratory depression because of actions at different receptor sites in the CNS that control respiration. Benzodiazepines interact at GABAA sites and opioids interact primarily at mu receptors. When benzodiazepines and opioids are combined, the potential for benzodiazepines to significantly worsen opioid-related respiratory depression exists. Limit dosage and duration of concomitant use of benzodiazepines and opioids, and monitor patients closely for respiratory depression and sedation. Monitor patients closely for respiratory depression and sedation.

Other CNS depressants

The sedative effect of intravenous midazolam is accentuated by any concomitantly administered medication, which depresses the central nervous system, particularly opioids (e.g., morphine, meperidine and fentanyl) and also secobarbital and droperidol. Consequently, the dosage of midazolam should be adjusted according to the type and amount of concomitant medications administered and the desired clinical response (see DOSAGE AND ADMINISTRATION).

Other Drug Interactions

Caution is advised when midazolam is administered concomitantly with drugs that are known to inhibit the P450-3A4 enzyme system such as cimetidine (not ranitidine), erythromycin, diltiazem, verapamil, ketoconazole and itraconazole. These drug interactions may result in prolonged sedation due to a decrease in plasma clearance of midazolam.

The effect of single oral doses of 800 mg cimetidine and 300 mg ranitidine on steady-state concentrations of oral midazolam was examined in a randomized crossover study (n=8). Cimetidine increased the mean midazolam steady-state concentration from 57 to 71 ng/mL. Ranitidine increased the mean steady-state concentration to 62 ng/mL. No change in choice reaction time or sedation index was detected after dosing with the H2 receptor antagonists.

In a placebo-controlled study, erythromycin administered as a 500 mg dose, three times a day, for 1 week (n=6), reduced the clearance of midazolam following a single 0.5 mg/kg intravenous dose. The half-life was approximately doubled.

Caution is advised when midazolam is administered to patients receiving erythromycin since this may result in a decrease in the plasma clearance of midazolam.

The effects of diltiazem (60 mg three times a day) and verapamil (80 mg three times a day) on the pharmacokinetics and pharmacodynamics of midazolam were investigated in a three-way crossover study (n=9). The half-life of midazolam increased from 5 to 7 hours when midazolam was taken in conjunction with verapamil or diltiazem. No interaction was observed in healthy subjects between midazolam and nifedipine.

In a placebo-controlled study, where saquinavir or placebo was administered orally as a 1200 mg dose, three times a day, for 5 days (n=12), a 56% reduction in the clearance of midazolam following a single 0.05 mg/kg intravenous dose was observed. The half-life was approximately doubled.

A moderate reduction in induction dosage requirements of thiopental (about 15%) has been noted following use of intramuscular midazolam for premedication in adults.

The intravenous administration of midazolam decreases the minimum alveolar concentration (MAC) of halothane required for general anesthesia. This decrease correlates with the dose of midazolam administered; no similar studies have been carried out in pediatric patients but there is no scientific reason to expect that pediatric patients would respond differently than adults.

Although the possibility of minor interactive effects has not been fully studied, midazolam and pancuronium have been used together in patients without noting clinically significant changes in dosage, onset or duration in adults. Midazolam does not protect against the characteristic circulatory changes noted after administration of succinylcholine or pancuronium and does not protect against the increased intracranial pressure noted following administration of succinylcholine. Midazolam does not cause a clinically significant change in dosage, onset or duration of a single intubating dose of succinylcholine; no similar studies have been carried out in pediatric patients but there is no scientific reason to expect that pediatric patients would respond differently than adults.

No significant adverse interactions with commonly used premedications or drugs used during anesthesia and surgery (including atropine, scopolamine, glycopyrrolate, diazepam, hydroxyzine, d-tubocurarine, succinylcholine and other nondepolarizing muscle relaxants) or topical local anesthetics (including lidocaine, dyclonine HCl and Cetacaine) have been observed in adults or pediatric patients. In neonates, however, severe hypotension has been reported with concomitant administration of fentanyl. This effect has been observed in neonates on an infusion of midazolam who received a rapid injection of fentanyl and in patients on an infusion of fentanyl who have received a rapid injection of midazolam.

DRUG AND OR LABORATORY TEST INTERACTIONS

Drug/Laboratory Test Interactions: Midazolam has not been shown to interfere with results obtained in clinical laboratory tests.

Carcinogenesis, Mutagenesis, Impairment of Fertility:

Carcinogenesis: Midazolam maleate was administered with diet in mice and rats for 2 years at dosages of 1, 9 and 80 mg/kg/day. In female mice in the highest dose group there was a marked increase in the incidence of hepatic tumors. In high-dose male rats there was a small but statistically significant increase in benign thyroid follicular cell tumors. Dosages of 9 mg/kg/day of midazolam maleate (4 times a human induction dose of 0.35 mg/kg based on body surface area comparison) do not increase the incidence of tumors. The pathogenesis of induction of these tumors is not known. These tumors were found after chronic administration, whereas human use will ordinarily be of single or several doses.

Mutagenesis: Midazolam did not have mutagenic activity in Salmonella typhimurium (5 bacterial strains), Chinese hamster lung cells (V79), human lymphocytes or in the micronucleus test in mice.

Impairment of Fertility: Male rats were treated orally with 1, 4, or 16 mg/kg midazolam beginning 62 days prior to mating with female rats treated with the same doses for 14 days prior to mating to Gestation Day 13 or Lactation Day 21. The high dose produced an equivalent exposure (AUC) as 4 mg/kg intravenous midazolam (1.85 times the human induction dose of 0.35 mg/kg based on body surface area comparison). There were no adverse effects on either male or female fertility noted.

Pregnancy

Risk Summary

Neonates born to mothers using benzodiazepines late in pregnancy have been reported to experience symptoms of sedation and/or neonatal withdrawal (see WARNINGS: Neonatal Sedation and Withdrawal Syndrome, and PRECAUTIONS: Clinical Considerations). Available data from published observational studies of pregnant women exposed to benzodiazepines do not report a clear association with benzodiazepines and major birth defects (see Data).

The background risk of major birth defects and miscarriage for the indicated population is unknown. All pregnancies have a background risk of birth defect, loss, or other adverse outcomes. In the U.S. general population, the estimated risk of major birth defects and of miscarriage in clinically recognized pregnancies is 2 to 4% and 15 to 20%, respectively.

Clinical Considerations

Fetal/Neonatal Adverse Reactions

Benzodiazepines cross the placenta and may produce respiratory depression, hypotonia, and sedation in neonates. Monitor neonates exposed to midazolam injection during pregnancy or labor for signs of sedation, respiratory depression, hypotonia, and feeding problems. Monitor neonates exposed to midazolam injection during pregnancy for signs of withdrawal. Manage these neonates accordingly (see WARNINGS: Neonatal Sedation and Withdrawal Syndrome).

Data

Human Data

Published data from observational studies on the use of benzodiazepines during pregnancy do not report a clear association with benzodiazepines and major birth defects.

Although early studies reported an increased risk of congenital malformations with diazepam and chlordiazepoxide, there was no consistent pattern noted. In addition, the majority of more recent case-control and cohort studies of benzodiazepine use during pregnancy, which were adjusted for confounding exposures to alcohol, tobacco and other medications, have not confirmed these findings.

Animal Data

Pregnant rats were treated with midazolam using intravenous doses of 0.2, 1, and 4 mg/kg/day (0.09, 0.46, and 1.85 times the human induction dose of 0.35 mg/kg based on body surface area comparisons) during the period of organogenesis (Gestation Day 7 through 15). Midazolam did not cause adverse effects to the fetus at doses of up to 1.85 times the human induction dose. All doses produced slight to moderate ataxia. The high dose produced a 5% decrease in maternal body weight gain compared to control.

Pregnant rabbits were treated with midazolam using intravenous doses of 0.2, 0.6, and 2 mg/kg/day (0.09, 0.46, and 1.85 times the human induction dose of 0.35 mg/kg based on body surface area comparisons) during the period of organogenesis (Gestation Day 7 to 18). Midazolam did not cause adverse effects to the fetus at doses of up to 1.85 times the human induction dose. The high dose was associated with findings of ataxia and sedation but no evidence of maternal toxicity.

Pregnant rats were administered midazolam using intravenous doses of 0.2, 1, and 4 mg/kg/day (0.09, 0.46, and 1.85 times the human induction dose of 0.35 mg/kg based on body surface area comparisons) during late gestation and through lactation (Gestation Day 15 through Lactation Day 21). All doses produced ataxia. The high dose produced a slight decrease in maternal body weight gain compared to control. There were no clear adverse effects noted in the offspring. The study included no functional assessments of the pups, such as learning and memory testing or reproductive capacity.

In a published study in primates, administration of an anesthetic dose of ketamine for 24 hours on Gestation Day 122 increased neuronal apoptosis in the developing brain of the fetus. In other published studies, administration of either isoflurane or propofol for 5 hours on Gestation Day 120 resulted in increased neuronal and oligodendrocyte apoptosis in the developing brain of the offspring. With respect to brain development, this time period corresponds to the third trimester of gestation in the human. The clinical significance of these findings is not clear; however, studies in juvenile animals suggest neuroapoptosis correlates with long-term cognitive deficits (see WARNINGS, Pediatric Neurotoxicity, PRECAUTIONS, Pediatric Use and ANIMAL TOXICOLOGY AND/OR PHARMACOLOGY).

Nursing Mothers

Risk Summary

There are reports of sedation, poor feeding and poor weight gain in infants exposed to benzodiazepines through breast milk. Based on data from published studies, midazolam is present in human milk in low levels. There are no data on the effects of midazolam on milk production.

The developmental and health benefits of breastfeeding should be considered along with the mother's clinical need for midazolam injection and any potential adverse effects on the breastfed infant from midazolam injection or from the underlying maternal condition.

Clinical Considerations

Infants exposed to midazolam injection through breast milk should be monitored for sedation, poor feeding and poor weight gain. A lactating woman may consider interrupting breastfeeding and pumping and discarding breast milk during treatment for a range of at least 4 to 8 hours after midazolam administration in order to minimize drug exposure to a breastfed infant.

PEDIATRIC USE

Pediatric Use: The safety and efficacy of midazolam for sedation/anxiolysis/amnesia following single dose intramuscular administration, intravenously by intermittent injections and continuous infusion have been established in pediatric and neonatal patients. For specific safety monitoring and dosage guidelines (see Boxed WARNING, CLINICAL PHARMACOLOGY, INDICATIONS AND USAGE, WARNINGS, PRECAUTIONS, ADVERSE REACTIONS, OVERDOSAGE and DOSAGE AND ADMINISTRATION). UNLIKE ADULT PATIENTS, PEDIATRIC PATIENTS GENERALLY RECEIVE INCREMENTS OF MIDAZOLAM ON A MG/KG BASIS. As a group, pediatric patients generally require higher dosages of midazolam (mg/kg) than do adults. Younger (less than six years) pediatric patients may require higher dosages (mg/kg) than older pediatric patients, and may require closer monitoring. In obese PEDIATRIC PATIENTS, the dose should be calculated based on ideal body weight. When midazolam is given in conjunction with opioids or other sedatives, the potential for respiratory depression, airway obstruction, or hypoventilation is increased. The health care practitioner who uses this medication in pediatric patients should be aware of and follow accepted professional guidelines for pediatric sedation appropriate to their situation.

Midazolam should not be administered by rapid injection in the neonatal population. Severe hypotension and seizures have been reported following rapid intravenous administration, particularly, with concomitant use of fentanyl.

Midazolam injection contains benzyl alcohol as a preservative. Benzyl alcohol, a component of this product, has been associated with serious adverse events and death, particularly in pediatric patients. The "gasping syndrome", (characterized by central nervous system depression, metabolic acidosis, gasping respirations, and high levels of benzyl alcohol and its metabolites found in the blood and urine) has been associated with benzyl alcohol dosages greater than 99 mg/kg/day in neonates and low-birth-weight neonates. Additional symptoms may include gradual neurological deterioration, seizures, intracranial hemorrhage, hematologic abnormalities, skin breakdown, hepatic and renal failure, hypotension, bradycardia, and cardiovascular collapse. Although normal therapeutic doses of this product deliver amounts of benzyl alcohol that are substantially lower than those reported in association with the "gasping syndrome", the minimum amount of benzyl alcohol at which toxicity may occur is not known. Premature and low-birth-weight infants, as well as patients receiving high dosages, may be more likely to develop toxicity. Practitioners administering this and other medications containing benzyl alcohol should consider the combined daily metabolic load of benzyl alcohol from all sources.

Animal Data

Published juvenile animal studies demonstrate that the administration of anesthetic and sedation drugs, such as Midazolam Injection, USP, that either block NMDA receptors or potentiate the activity of GABA during the period of rapid brain growth or synaptogenesis, results in widespread neuronal and oligodendrocyte cell loss in the developing brain and alterations in synaptic morphology and neurogenesis. Based on comparisons across species, the window of vulnerability to these changes is believed to correlate with exposures in the third trimester of gestation through the first several months of life, but may extend out to approximately 3 years of age in humans.

In primates, exposure to 3 hours of ketamine that produced a light surgical plane of anesthesia did not increase neuronal cell loss, however, treatment regimens of 5 hours or longer of isoflurane increased neuronal cell loss. Data from isoflurane-treated rodents and ketamine-treated primates suggest that the neuronal and oligodendrocyte cell losses are associated with prolonged cognitive deficits in learning and memory. The clinical significance of these nonclinical findings is not known, and healthcare providers should balance the benefits of appropriate anesthesia in pregnant women, neonates, and young children who require procedures with the potential risks suggested by the nonclinical data (see WARNINGS, Pediatric Neurotoxicity, PRECAUTIONS, Pregnancy and ANIMAL TOXICOLOGY AND/OR PHARMACOLOGY).

GERIATRIC USE

Geriatric Use: Because geriatric patients may have altered drug distribution and diminished hepatic and/or renal function, reduced doses of midazolam are recommended. Intravenous and intramuscular midazolam should be decreased for elderly and for debilitated patients (see WARNINGS and DOSAGE AND ADMINISTRATION) and subjects over 70 years of age may be particularly sensitive. These patients will also probably take longer to recover completely after midazolam administration for the induction of anesthesia. Administration of intramuscular and intravenous midazolam to elderly and/or high risk surgical patients has been associated with rare reports of death under circumstances compatible with cardiorespiratory depression. In most of these cases, the patients also received other central nervous system depressants capable of depressing respiration, especially narcotics (see DOSAGE AND ADMINISTRATION).

Specific dosing and monitoring guidelines for geriatric patients are provided in the DOSAGE AND ADMINISTRATION section for premedicated patients for sedation/anxiolysis/amnesia following intravenous and intramuscular administration, for induction of anesthesia following intravenous administration and for continuous infusion.

ADVERSE REACTIONS

See WARNINGS concerning serious cardiorespiratory events and possible paradoxical reactions. Fluctuations in vital signs were the most frequently seen findings following parenteral administration of midazolam in adults and included decreased tidal volume and/or respiratory rate decrease (23.3% of patients following intravenous and 10.8% of patients following intramuscular administration) and apnea (15.4% of patients following intravenous administration), as well as variations in blood pressure and pulse rate. The majority of serious adverse effects, particularly those associated with oxygenation and ventilation, have been reported when midazolam is administered with other medications capable of depressing the central nervous system. The incidence of such events is higher in patients undergoing procedures involving the airway without the protective effect of an endotracheal tube, e.g., upper endoscopy and dental procedures.

Adults: The following additional adverse reactions were reported after intramuscular administration:

 | headache (1.3%) | Local effects at intramuscular Injection site pain (3.7%) induration (0.5%) redness (0.5%) muscle stiffness (0.3%)

Administration of intramuscular midazolam to elderly and/or higher risk surgical patients has been associated with rare reports of death under circumstances compatible with cardiorespiratory depression. In most of these cases, the patients also received other central nervous system depressants capable of depressing respiration, especially narcotics (see DOSAGE AND ADMINISTRATION).

The following additional adverse reactions were reported subsequent to intravenous administration as a single sedative/anxiolytic/amnestic agent in adult patients:

hiccoughs (3.9%)
nausea (2.8%)
vomiting (2.6%)
coughing (1.3%)
"oversedation" (1.6%)
headache (1.5%)
drowsiness (1.2%)

Local effects at the intravenous site
tenderness (5.6%)
pain during injection (5.0%)
redness (2.6%)
induration (1.7%)
phlebitis (0.4%)

Pediatric Patients: The following adverse events related to the use of intravenous midazolam in pediatric patients were reported in the medical literature: desaturation 4.6%, apnea 2.8%, hypotension 2.7%, paradoxical reactions 2.0%, hiccough 1.2 %, seizure-like activity 1.1% and nystagmus 1.1%. The majority of airway-related events occurred in patients receiving other CNS depressing medications and in patients where midazolam was not used as a single sedating agent.

Neonates: For information concerning hypotensive episodes and seizures following the administration of midazolam to neonates, (see Boxed WARNING, CONTRAINDICATIONS, WARNINGS and PRECAUTIONS).

Other adverse experiences, observed mainly following intravenous injection as a single sedative/anxiolytic/amnesia agent and occurring at an incidence of <1.0% in adult and pediatric patients, are as follows:

Respiratory: Laryngospasm, bronchospasm, dyspnea, hyperventilation, wheezing, shallow respirations, airway obstruction, tachypnea

Cardiovascular: Bigeminy, premature ventricular contractions, vasovagal episode, bradycardia, tachycardia, nodal rhythm

Gastrointestinal: Acid taste, excessive salivation, retching

CNS/Neuromuscular: Retrograde amnesia, euphoria, hallucination, confusion, argumentativeness, nervousness, anxiety, grogginess, restlessness, emergence delirium or agitation, prolonged emergence from anesthesia, dreaming during emergence, sleep disturbance, insomnia, nightmares, athetoid movements, seizure-like activity, ataxia, dizziness, dysphoria, slurred speech, dysphonia, paresthesia

Special Senses: Blurred vision, diplopia, nystagmus, pinpoint pupils, cyclic movements of eyelids, visual disturbance, difficulty focusing eyes, ears blocked, loss of balance, light-headedness

Integumentary: Hive-like elevation at injection site, swelling or feeling of burning, warmth or coldness at injection site

Hypersensitivity: Allergic reactions including anaphylactoid reactions, hives, rash, pruritus

Miscellaneous: Yawning, lethargy, chills, weakness, toothache, faint feeling, hematoma

DRUG ABUSE AND DEPENDENCE

Midazolam Injection contains midazolam a Schedule IV control substance.

Midazolam was actively self-administered in primate models used to assess the positive reinforcing effects of psychoactive drugs.

Midazolam produced physical dependence of a mild to moderate intensity in cynomolgus monkeys after 5 to 10 weeks of administration. Available data concerning the drug abuse and dependence potential of midazolam suggest that its abuse potential is at least equivalent to that of diazepam.

Withdrawal symptoms, similar in character to those noted with barbiturates and alcohol (convulsions, hallucinations, tremor, abdominal and muscle cramps, vomiting and sweating), have occurred following abrupt discontinuation of benzodiazepines, including midazolam. Abdominal distention, nausea, vomiting, and tachycardia are prominent symptoms of withdrawal in infants. The more severe withdrawal symptoms have usually been limited to those patients who had received excessive doses over an extended period of time. Generally milder withdrawal symptoms (e.g., dysphoria and insomnia) have been reported following abrupt discontinuance of benzodiazepines taken continuously at therapeutic levels for several months. Consequently, after extended therapy, abrupt discontinuation should generally be avoided and a gradual dosage tapering schedule followed. There is no consensus in the medical literature regarding tapering schedules; therefore, practitioners are advised to individualize therapy to meet patient's needs. In some case reports, patients who have had severe withdrawal reactions due to abrupt discontinuation of high-dose long-term midazolam, have been successfully weaned off of midazolam over a period of several days.

OVERDOSAGE

Clinical Presentation

Overdosage of benzodiazepines is characterized by central nervous system depression ranging from drowsiness to coma. In mild to moderate cases, symptoms can include drowsiness, confusion, dysarthria, lethargy, hypnotic state, diminished reflexes, ataxia, and hypotonia. Rarely, paradoxical or disinhibitory reactions (including agitation, irritability, impulsivity, violent behavior, confusion, restlessness, excitement, and talkativeness) may occur. In severe overdosage cases, patients may develop respiratory depression and coma. Overdosage of benzodiazepines in combination with other CNS depressants (including alcohol and opioids) may be fatal (see WARNINGS: Risks from Concomitant Use With Opioids, and Concomitant Use of Central Nervous System Depressants). Markedly abnormal (lowered or elevated) blood pressure, heart rate, or respiratory rate raise the concern that additional drugs and/or alcohol are involved in the overdosage.

Management of Overdose

In managing benzodiazepine overdosage, employ general supportive measures, including intravenous fluids and airway maintenance. Flumazenil, a specific benzodiazepine receptor antagonist indicated for the complete or partial reversal of the sedative effects of benzodiazepines in the management of benzodiazepine overdosage, can lead to withdrawal and adverse reactions, including seizures, particularly in the context of mixed overdosage with drugs that increase seizure risk (e.g., tricyclic and tetracyclic antidepressants) and in patients with long-term benzodiazepine use and physical dependency. The risk of withdrawal seizures with flumazenil use may be increased in patients with epilepsy. Flumazenil is contraindicated in patients who have received a benzodiazepine for control of a potentially life-threatening condition (e.g., status epilepticus). If the decision is made to use flumazenil, it should be used as an adjunct to, not as a substitute for, supportive management of benzodiazepine overdosage. See the flumazenil injection Prescribing Information.

Consider contacting a poison center (1-800-222-1222), poisoncontrol.org, or a medical toxicologist for additional overdosage management recommendations.

DOSAGE AND ADMINISTRATION

NOTE: CONTAINS BENZYL ALCOHOL (see WARNINGS and PRECAUTIONS, Pediatric Use)

Midazolam injection is a potent sedative agent that requires slow administration and individualization of dosage. Clinical experience has shown midazolam to be 3 to 4 times as potent per mg as diazepam. BECAUSE SERIOUS AND LIFE-THREATENING CARDIORESPIRATORY ADVERSE EVENTS HAVE BEEN REPORTED, PROVISION FOR MONITORING, DETECTION AND CORRECTION OF THESE REACTIONS MUST BE MADE FOR EVERY PATIENT TO WHOM MIDAZOLAM INJECTION IS ADMINISTERED, REGARDLESS OF AGE OR HEALTH STATUS. Excessive single doses or rapid intravenous administration may result in respiratory depression, airway obstruction and/or arrest. The potential for these latter effects is increased in debilitated patients, those receiving concomitant medications capable of depressing the CNS, and patients without an endotracheal tube but undergoing a procedure involving the upper airway such as endoscopy or dental (see Boxed WARNING and WARNINGS).

Reactions such as agitation, involuntary movements, hyperactivity and combativeness have been reported in adult and pediatric patients. Should such reactions occur, caution should be exercised before continuing administration of midazolam (see WARNINGS).

Midazolam injection should only be administered intramuscularly or intravenously (see WARNINGS).

Care should be taken to avoid intra-arterial injection or extravasation (see WARNINGS).

Midazolam Injection may be mixed in the same syringe with the following frequently used premedications: morphine sulfate, meperidine, atropine sulfate or scopolamine. Midazolam, at a concentration of 0.5 mg/mL, is compatible with 5% dextrose in water and 0.9% sodium chloride for up to 24 hours and with lactated Ringer's solution for up to 4 hours. Both the 1 mg/mL and 5 mg/mL formulations of midazolam may be diluted with 0.9% sodium chloride or 5% dextrose in water.

Monitoring: Patient response to sedative agents, and resultant respiratory status, is variable. Regardless of the intended level of sedation or route of administration, sedation is a continuum; a patient may move easily from light to deep sedation, with potential loss of protective reflexes. This is especially true in pediatric patients. Sedative doses should be individually titrated, taking into account patient age, clinical status and concomitant use of other CNS depressants. Continuous monitoring of respiratory and cardiac function is required (i.e., pulse oximetry).

Adults and Pediatrics: Sedation guidelines recommend a careful presedation history to determine how a patient's underlying medical conditions or concomitant medications might affect their response to sedation/analgesia as well as a physical examination including a focused examination of the airway for abnormalities. Further recommendations include appropriate presedation fasting.

Titration to effect with multiple small doses is essential for safe administration. It should be noted that adequate time to achieve peak central nervous system effect (3 to 5 minutes) for midazolam should be allowed between doses to minimize the potential for oversedation. Sufficient time must elapse between doses of concomitant sedative medications to allow the effect of each dose to be assessed before subsequent drug administration. This is an important consideration for all patients who receive intravenous midazolam.

Immediate availability of resuscitative drugs and age- and size-appropriate equipment and personnel trained in their use and skilled in airway management should be assured (see WARNINGS).

Pediatrics: For deeply sedated pediatric patients a dedicated individual, other than the practitioner performing the procedure, should monitor the patient throughout the procedure.

Intravenous access is not thought to be necessary for all pediatric patients sedated for a diagnostic or therapeutic procedure because in some cases the difficulty of gaining intravenous access would defeat the purpose of sedating the child; rather, emphasis should be placed upon having the intravenous equipment available and a practitioner skilled in establishing vascular access in pediatric patients immediately available.

USUAL ADULT DOSE
INTRAMUSCULARLY
For preoperative sedation/anxiolysis/amnesia (induction of sleepiness or drowsiness and relief of apprehension and to impair memory of perioperative events). For intramuscular use, midazolam should be injected deep in a large muscle mass. | The recommended premedication dose of midazolam for good risk (ASA Physical Status I & II) adult patients below the age of 60 years is 0.07 to 0.08 mg/kg intramuscular (approximately 5 mg intramuscular) administered up to 1 hour before surgery. The dose must be individualized and reduced when intramuscular midazolam is administered to patients with chronic obstructive pulmonary disease, other higher risk surgical patients, patients 60 or more years of age, and patients who have received concomitant narcotics or other CNS depressants (see ADVERSE REACTIONS). In a study of patients 60 years or older, who did not receive concomitant administration of narcotics, 2 to 3 mg (0.02 to 0.05 mg/kg) of midazolam produced adequate sedation during the preoperative period. The dose of 1 mg intramuscular midazolam may suffice for some older patients if the anticipated intensity and duration of sedation is less critical. As with any potential respiratory depressant, these patients require observation for signs of cardiorespiratory depression after receiving intramuscular midazolam. Onset is within 15 minutes, peaking at 30 to 60 minutes. It can be administered concomitantly with atropine sulfate or scopolamine and reduced doses of narcotics.
INTRAVENOUSLY
Sedation/anxiolysis/amnesia for procedures (see INDICATIONS AND USAGE): Narcotic premedication results in less variability in patient response and a reduction in dosage of midazolam. For peroral procedures, the use of an appropriate topical anesthetic is recommended. For bronchoscopic procedures, the use of narcotic premedication is recommended. | When used for sedation/anxiolysis/amnesia for a procedure, dosage must be individualized and titrated. Midazolam should always be titrated slowly; administer over at least 2 minutes and allow an additional 2 or more minutes to fully evaluate the sedative effect. Individual response will vary with age, physical status and concomitant medications, but may also vary independent of these factors (see WARNINGS concerning cardiac/respiratory arrest/airway obstruction/hypoventilation).
Midazolam 1 mg/mL formulation is recommended for sedation/anxiolysis/amnesia for procedures to facilitate slower injection. Both the 1 mg/mL and the 5 mg/mL formulations may be diluted with 0.9% sodium chloride or 5% dextrose in water. | 1. Healthy Adults Below the Age of 60: Titrate slowly to the desired effect, e.g., the initiation of slurred speech. Some patients may respond to as little as 1 mg. No more than 2.5 mg should be given over a period of at least 2 minutes. Wait an additional 2 or more minutes to fully evaluate the sedative effect. If further titration is necessary, continue to titrate, using small increments, to the appropriate level of sedation. Wait an additional 2 or more minutes after each increment to fully evaluate the sedative effect. A total dose greater than 5 mg is not usually necessary to reach the desired endpoint. If narcotic premedication or other CNS depressants are used, patients will require approximately 30% less midazolam than unpremedicated patients. 2. Patients Age 60 or Older, and Debilitated or Chronically Ill Patients: Because the danger of hypoventilation, airway obstruction, or apnea is greater in elderly patients and those with chronic disease states or decreased pulmonary reserve, and because the peak effect may take longer in these patients, increments should be smaller and the rate of injection slower. Titrate slowly to the desired effect, e.g., the initiation of slurred speech. Some patients may respond to as little as 1 mg. No more than 1.5 mg should be given over a period of no less than 2 minutes. Wait an additional 2 or more minutes to fully evaluate the sedative effect. If additional titration is necessary, it should be given at a rate of no more than 1 mg over a period of 2 minutes, waiting an additional 2 or more minutes each time to fully evaluate the sedative effect. Total doses greater than 3.5 mg are not usually necessary. If concomitant CNS depressant premedications are used in these patients, they will require at least 50% less midazolam than healthy young unpremedicated patients. 3. Maintenance Dose: Additional doses to maintain the desired level of sedation may be given in increments of 25% of the dose used to first reach the sedative endpoint, but again only by slow titration, especially in the elderly and chronically ill or debilitated patient. These additional doses should be given only after a thorough clinical evaluation clearly indicates the need for additional sedation.
Induction of Anesthesia:; For induction of general anesthesia, before administration of other anesthetic agents. | Individual response to the drug is variable, particularly when a narcotic premedication is not used. The dosage should be titrated to the desired effect according to the patient's age and clinical status. When midazolam is used before other intravenous agents for induction of anesthesia, the initial dose of each agent may be significantly reduced, at times to as low as 25% of the usual initial dose of the individual agents. Unpremedicated Patients: In the absence of premedication, an average adult under the age of 55 years will usually require an initial dose of 0.3 to 0.35 mg/kg for induction, administered over 20 to 30 seconds and allowing 2 minutes for effect. If needed to complete induction, increments of approximately 25% of the patient's initial dose may be used; induction may instead be completed with inhalational anesthetics. In resistant cases, up to 0.6 mg/kg total dose may be used for induction, but such larger doses may prolong recovery. Unpremedicated patients over the age of 55 years usually require less midazolam for induction; an initial dose of 0.3 mg/kg is recommended. Unpremedicated patients with severe systemic disease or other debilitation usually require less midazolam for induction. An initial dose of 0.2 to 0.25 mg/kg will usually suffice; in some cases, as little as 0.15 mg/kg may suffice. Premedicated Patients: When the patient has received sedative or narcotic premedication, particularly narcotic premedication, the range of recommended doses is 0.15 to 0.35 mg/kg. In average adults below the age of 55 years, a dose of 0.25 mg/kg, administered over 20 to 30 seconds and allowing 2 minutes for effect, will usually suffice. The initial dose of 0.2 mg/kg is recommended for good risk (ASA I & II) surgical patients over the age of 55 years. In some patients with severe systemic disease or debilitation, as little as 0.15 mg/kg may suffice. Narcotic premedication frequently used during clinical trials included fentanyl (1.5 to 2 mcg/kg intravenous, administered 5 minutes before induction), morphine (dosage individualized, up to 0.15 mg/kg intramuscular), and meperidine (dosage individualized, up to 1 mg/kg intramuscular). Sedative premedications were hydroxyzine pamoate (100 mg orally) and sodium secobarbital (200 mg orally). Except for intravenous fentanyl, administered 5 minutes before induction, all other premedications should be administered approximately 1 hour prior to the time anticipated for midazolam induction.
Injectable midazolam can also be used during maintenance of anesthesia, for surgical procedures, as a component of balanced anesthesia. Effective narcotic premedication is especially recommended in such cases. | Incremental injections of approximately 25% of the induction dose should be given in response to signs of lightening of anesthesia and repeated as necessary.
CONTINUOUS INFUSION
For continuous infusion, midazolam 5 mg/mL formulation is recommended diluted to a concentration of 0.5 mg/mL with 0.9% sodium chloride or 5% dextrose in water. | Usual Adult Dose: If a loading dose is necessary to rapidly initiate sedation, 0.01 to 0.05 mg/kg (approximately 0.5 to 4 mg for a typical adult) may be given slowly or infused over several minutes. This dose may be repeated at 10 to 15 minute intervals until adequate sedation is achieved. For maintenance of sedation, the usual initial infusion rate is 0.02 to 0.10 mg/kg/hr (1 to 7 mg/hr). Higher loading or maintenance infusion rates may occasionally be required in some patients. The lowest recommended doses should be used in patients with residual effects from anesthetic drugs, or in those concurrently receiving other sedatives or opioids. Individual response to midazolam is variable. The infusion rate should be titrated to the desired level of sedation, taking into account the patient's age, clinical status and current medications. In general, midazolam should be infused at the lowest rate that produces the desired level of sedation. Assessment of sedation should be performed at regular intervals and the midazolam infusion rate adjusted up or down by 25% to 50% of the initial infusion rate so as to assure adequate titration of sedation level. Larger adjustments or even a small incremental dose may be necessary if rapid changes in the level of sedation are indicated. In addition, the infusion rate should be decreased by 10% to 25% every few hours to find the minimum effective infusion rate. Finding the minimum effective infusion rate decreases the potential accumulation of midazolam and provides for the most rapid recovery once the infusion is terminated. Patients who exhibit agitation, hypertension, or tachycardia in response to noxious stimulation, but who are otherwise adequately sedated, may benefit from concurrent administration of an opioid analgesic. Addition of an opioid will generally reduce the minimum effective midazolam infusion rate.
PEDIATRIC PATIENTS
 | UNLIKE ADULT PATIENTS, PEDIATRIC PATIENTS GENERALLY RECEIVE INCREMENTS OF MIDAZOLAM ON A MG/KG BASIS. As a group, pediatric patients generally require higher dosages of midazolam (mg/kg) than do adults. Younger (less than six years) pediatric patients may require higher dosages (mg/kg) than older pediatric patients, and may require close monitoring (see tables below). In obese PEDIATRIC PATIENTS, the dose should be calculated based on ideal body weight. When midazolam is given in conjunction with opioids or other sedatives, the potential for respiratory depression, airway obstruction, or hypoventilation is increased. For appropriate patient monitoring, see Boxed WARNING, WARNINGS, and DOSAGE AND ADMINISTRATION, MONITORING. The health care practitioner who uses this medication in pediatric patients should be aware of and follow accepted professional guidelines for pediatric sedation appropriate to their situation.

OBSERVER'S ASSESSMENT OF ALERTNESS/SEDATION (OAA/S)
Assessment Categories
Responsiveness | Speech | Facial Expression | Eyes | Composite Score
Responds readily to name spoken in normal tone | normal | normal | clear, no ptosis | 5 (alert)
Lethargic response to name spoken in normal tone | mild slowing or thickening | mild relaxation | glazed or mild ptosis (less than half the eye) | 4
Responds only after name is called loudly and/or repeatedly | slurring or prominent slowing | marked relaxation (slack jaw) | glazed and marked ptosis (half the eye or more) | 3
Responds only after mild prodding or shaking | few recognizable words | — | — | 2
Does not respond to mild prodding or shaking | — | — | — | 1 (deep sleep)

FREQUENCY OF OBSERVER'S ASSESSMENT OF ALERTNESS/SEDATION COMPOSITE SCORES IN ONE STUDY OF CHILDREN UNDERGOING PROCEDURES WITH INTRAVENOUS MIDAZOLAM FOR SEDATION
Age Range (years) | n | OAA/S Score
 |  | 1 (deep sleep) | 2 | 3 | 4 | 5 (alert)
1–2 | 16 | 6 (38%) | 4 (25%) | 3 (19%) | 3 (19%) | 0
>2–5 | 22 | 9 (41%) | 5 (23%) | 8 (36%) | 0 | 0
>5–12 | 34 | 1 (3%) | 6 (18%) | 22 (65%) | 5 (15%) | 0
>12–17 | 18 | 0 | 4 (22%) | 14 (78%) | 0 | 0
Total (1–17) | 90 | 16 (18%) | 19 (21%) | 47 (52%) | 8 (9%) | 0

INTRAMUSCULARLY | USUAL PEDIATRIC DOSE (NON-NEONATAL)
For sedation/anxiolysis/amnesia prior to anesthesia or for procedures, intramuscular midazolam can be used to sedate pediatric patients to facilitate less traumatic insertion of an intravenous catheter for titration of additional medication. | Sedation after intramuscular midazolam is age and dose dependent: higher doses may result in deeper and more prolonged sedation. Doses of 0.1 to 0.15 mg/kg are usually effective and do not prolong emergence from general anesthesia. For more anxious patients, doses up to 0.5 mg/kg have been used. Although not systematically studied, the total dose usually does not exceed 10 mg. If midazolam is given with an opioid, the initial dose of each must be reduced.
INTRAVENOUSLY BY INTERMITTENT INJECTION | USUAL PEDIATRIC DOSE (NON-NEONATAL)
For sedation/anxiolysis/amnesia prior to and during procedures or prior to anesthesia. | It should be recognized that the depth of sedation/anxiolysis needed for pediatric patients depends on the type of procedure to be performed. For example, simple light sedation/anxiolysis in the preoperative period is quite different from the deep sedation and analgesia required for an endoscopic procedure in a child. For this reason, there is a broad range of dosage. For all pediatric patients, regardless of the indications for sedation/anxiolysis, it is vital to titrate midazolam and other concomitant medications slowly to the desired clinical effect. The initial dose of midazolam should be administered over 2 to 3 minutes. Since midazolam is water soluble, it takes approximately three times longer than diazepam to achieve peak EEG effects, therefore one must wait an additional 2 to 3 minutes to fully evaluate the sedative effect before initiating a procedure or repeating a dose. If further sedation is necessary, continue to titrate with small increments until the appropriate level of sedation is achieved. If other medications capable of depressing the CNS are coadministered, the peak effect of those concomitant medications must be considered and the dose of midazolam adjusted. The importance of drug titration to effect is vital to the safe sedation/anxiolysis of the pediatric patient. The total dose of midazolam will depend on patient response, the type and duration of the procedure, as well as the type and dose of concomitant medications.; 1. Pediatric patients less than 6 months of age: Limited information is available in non-intubated pediatric patients less than 6 months of age. It is uncertain when the patient transfers from neonatal physiology to pediatric physiology, therefore the dosing recommendations are unclear. Pediatric patients less than 6 months of age are particularly vulnerable to airway obstruction and hypoventilation, therefore titration with small increments to clinical effect and careful monitoring are essential. 2. Pediatric patients 6 months to 5 years of age: Initial dose 0.05 to 0.1 mg/kg. A total dose up to 0.6 mg/kg may be necessary to reach the desired endpoint but usually does not exceed 6 mg. Prolonged sedation and risk of hypoventilation may be associated with the higher doses. 3. Pediatric patients 6 to 12 years of age: Initial dose 0.025 to 0.05 mg/kg; total dose up to 0.4 mg/kg may be needed to reach the desired endpoint but usually does not exceed 10 mg. Prolonged sedation and risk of hypoventilation may be associated with the higher doses. 4. Pediatric patients 12 to 16 years of age: Should be dosed as adults. Prolonged sedation may be associated with higher doses; some patients in this age range will require higher than recommended adult doses but the total dose usually does not exceed 10 mg.; The dose of midazolam must be reduced in patients premedicated with opioid or other sedative agents including midazolam. Higher risk or debilitated patients may require lower dosages whether or not concomitant sedating medications have been administered (see WARNINGS).
CONTINUOUS INTRAVENOUS INFUSION | USUAL PEDIATRIC DOSE (NON-NEONATAL)
For sedation/anxiolysis/amnesia in critical care settings. | To initiate sedation, an intravenous loading dose of 0.05 to 0.2 mg/kg administered over at least 2 to 3 minutes can be used to establish the desired clinical effect IN PATIENTS WHOSE TRACHEA IS INTUBATED. (Midazolam should not be administered as a rapid intravenous dose.) This loading dose may be followed by a continuous intravenous infusion to maintain the effect. An infusion of midazolam injection has been used in patients whose trachea was intubated but who were allowed to breathe spontaneously. Assisted ventilation is recommended for pediatric patients who are receiving other central nervous system depressant medications such as opioids. Based on pharmacokinetic parameters and reported clinical experience, continuous intravenous infusions of midazolam should be initiated at a rate of 0.06 to 0.12 mg/kg/hr (1 to 2 mcg/kg/min). The rate of infusion can be increased or decreased (generally by 25% of the initial or subsequent infusion rate) as required, or supplemental intravenous doses of midazolam can be administered to increase or maintain the desired effect. Frequent assessment at regular intervals using standard pain/sedation scales is recommended. Drug elimination may be delayed in patients receiving erythromycin and/or other P450-3A4 enzyme inhibitors (see PRECAUTIONS, Drug Interactions) and in patients with liver dysfunction, low cardiac output (especially those requiring inotropic support), and in neonates. Hypotension may be observed in patients who are critically ill, particularly those receiving opioids and/or when midazolam is rapidly administered. When initiating an infusion with midazolam in hemodynamically compromised patients, the usual loading dose of midazolam should be titrated in small increments and the patient monitored for hemodynamic instability, e.g., hypotension. These patients are also vulnerable to the respiratory depressant effects of midazolam and require careful monitoring of respiratory rate and oxygen saturation.
CONTINUOUS INTRAVENOUS INFUSION | USUAL NEONATAL DOSE
For sedation in critical care settings. | Based on pharmacokinetic parameters and reported clinical experience in preterm and term neonates WHOSE TRACHEA WAS INTUBATED, continuous intravenous infusions of midazolam injection should be initiated at a rate of 0.03 mg/kg/hr (0.5 mcg/kg/min) in neonates <32 weeks and 0.06 mg/kg/hr (1 mcg/kg/min) in neonates >32 weeks. Intravenous loading doses should not be used in neonates, rather the infusion may be run more rapidly for the first several hours to establish therapeutic plasma levels. The rate of infusion should be carefully and frequently reassessed, particularly after the first 24 hours so as to administer the lowest possible effective dose and reduce the potential for drug accumulation. This is particularly important because of the potential for adverse effects related to metabolism of the benzyl alcohol (see WARNINGS, Usage In Preterm Infants And Neonates). Hypotension may be observed in patients who are critically ill and in preterm and term infants, particularly those receiving fentanyl and/or when midazolam is administered rapidly. Due to an increased risk of apnea, extreme caution is advised when sedating preterm and former preterm patients whose trachea is not intubated.

NOTE: Parenteral drug products should be inspected visually for particulate matter and discoloration prior to administration, whenever solution and container permit.

HOW SUPPLIED

Product: 50090-5342

NDC: 50090-5342-0 10 mL in a VIAL / 10 in a BOX

NDC: 50090-5342-1 10 mL in a VIAL

ANIMAL TOXICOLOGY AND/OR PHARMACOLOGY

Published studies in animals demonstrate that the use of anesthetic agents during the period of rapid brain growth or synaptogenesis results in widespread neuronal and oligodendrocyte cell loss in the developing brain and alterations in synaptic morphology and neurogenesis. Based on comparisons across species, the window of vulnerability to these changes is believed to correlate with exposures in the third trimester through the first several months of life, but may extend out to approximately 3 years of age in humans.

In primates, exposure to 3 hours of an anesthetic regimen that produced a light surgical plane of anesthesia did not increase neuronal cell loss, however, treatment regimens of 5 hours or longer increased neuronal cell loss. Data in rodents and in primates suggest that the neuronal and oligodendrocyte cell losses are associated with subtle but prolonged cognitive deficits in learning and memory. The clinical significance of these nonclinical findings is not known, and healthcare providers should balance the benefits of appropriate anesthesia in neonates and young children who require procedures against the potential risks suggested by the nonclinical data (see WARNINGS, Pediatric Neurotoxicity and PRECAUTIONS, Pregnancy and Pediatric Use).

For more information concerning this drug, please call 1-800-438-1985 or visit www.pfizer.com.

To report SUSPECTED ADVERSE REACTIONS, please call 1-800-438-1985 or FDA at 1-800-FDA-1088 or www.fda.gov/medwatch.

Distributed by Hospira, Inc., Lake Forest, IL 60045 USA

LAB-0851-11.0
Revised: 1/2023